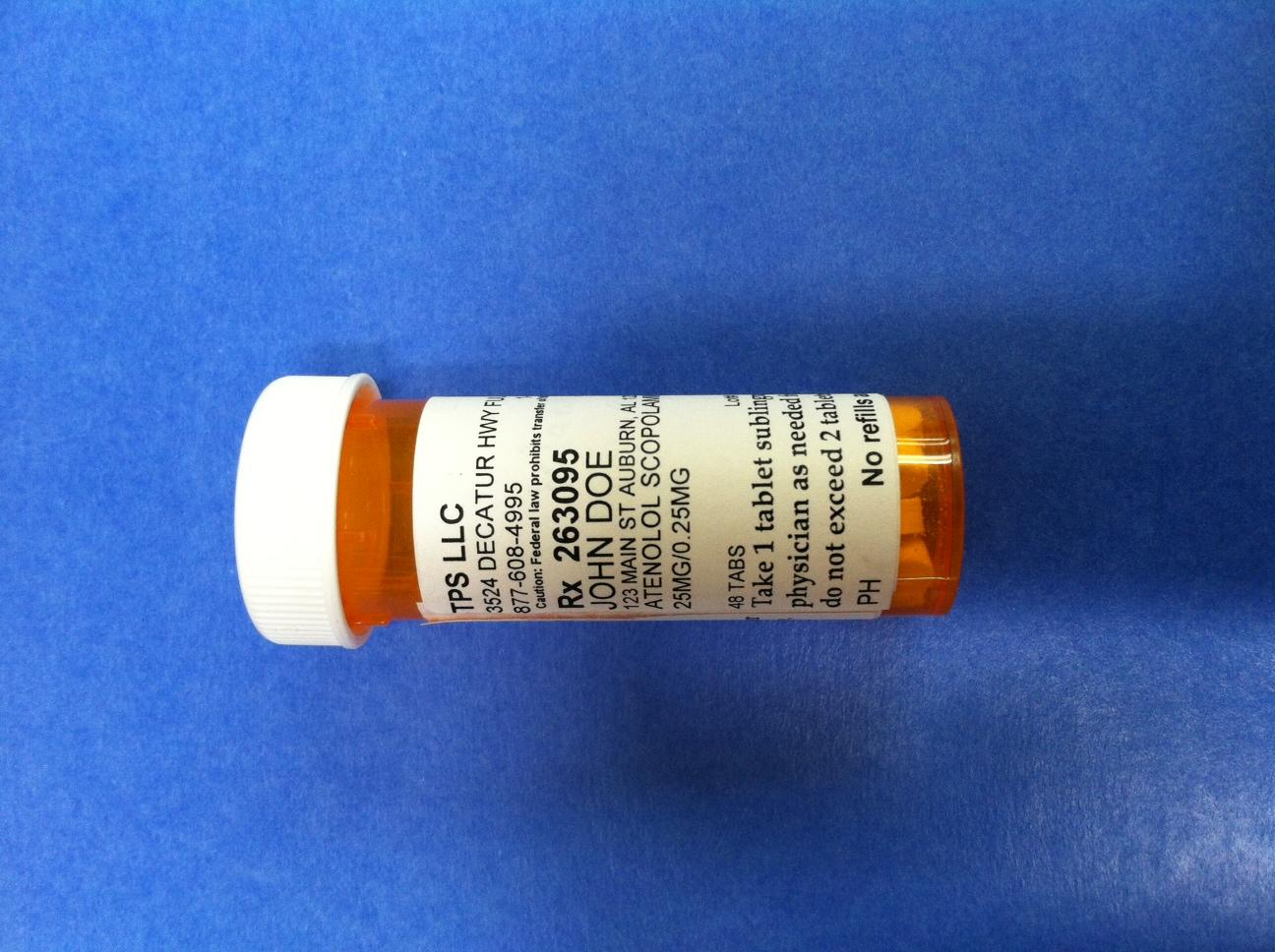 DRUG LABEL: Propranolol Scopolamine
NDC: 69267-201 | Form: TABLET
Manufacturer: TPS
Category: prescription | Type: HUMAN PRESCRIPTION DRUG LABEL
Date: 20141015

ACTIVE INGREDIENTS: SCOPOLAMINE HYDROBROMIDE .25 mg/20.25 mg; PROPRANOLOL HYDROCHLORIDE 20 mg/20.25 mg

INSTRUCTIONS FOR USE

Take one tablet orally as directed by your physician as needed for symptoms of panic or anxiety.

Do not exceed two tablets per day.

PACKAGE LABEL

TPS LLC

3524 DECATUR HWY FULTONDALE, AL 35068

877-608-4995 1-877-608-4995 BT9752747

Caution: Federal law prohibits transfer of this drug to any other person than patient for whom prescribed

Rx 263095 Jack Doe/Dr. Jane Doe MD

JOHN DOE

123 MAIN ST AUBURN, AL 12345

PROPRANOLOL SCOPOLAMINE TABLET TRITURATE

20 MG/0.25 MG

48 TABS Lot# Exp

Take 1 tablet sublingually or orally as directed by your physician as needed for symptoms of panic or anxiety.

Do not exceed 2 tablets per day

PH No refills authorized 10/8/2014

Pill bottle low res.jpg